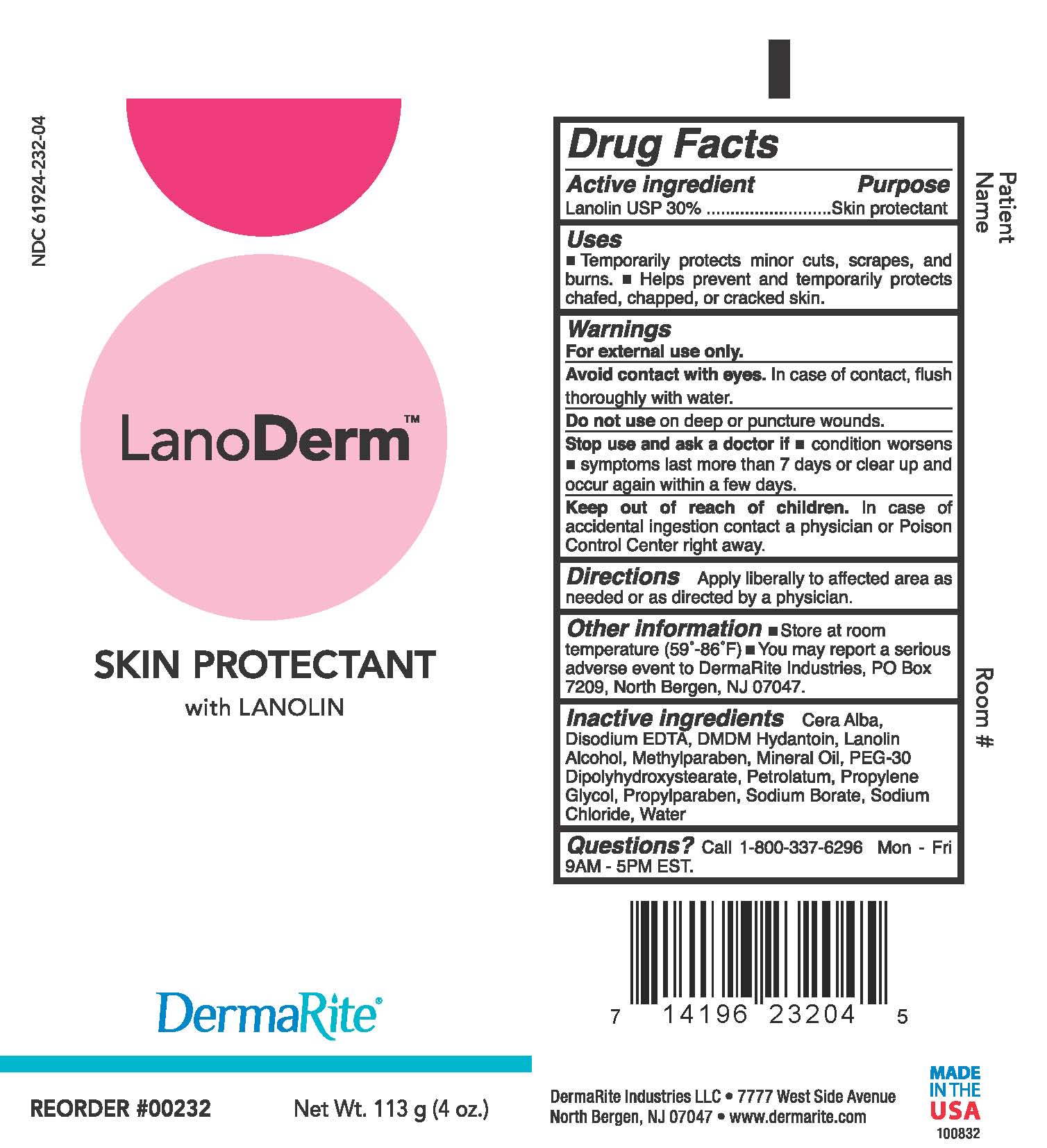 DRUG LABEL: Lanoderm
NDC: 61924-232 | Form: OINTMENT
Manufacturer: Dermarite Industries LLC
Category: otc | Type: HUMAN OTC DRUG LABEL
Date: 20180914

ACTIVE INGREDIENTS: LANOLIN 0.3 g/100 g
INACTIVE INGREDIENTS: PETROLATUM; MINERAL OIL; WHITE WAX; LANOLIN ALCOHOLS; PEG-30 DIPOLYHYDROXYSTEARATE; WATER; SODIUM BORATE; SODIUM CHLORIDE; EDETATE DISODIUM; DMDM HYDANTOIN; METHYLPARABEN; PROPYLENE GLYCOL; PROPYLPARABEN

DRUG LISTING: LANODERM

Active Ingredient:

Lanolin USP 30%

Purpose:

Skin Protectant

Uses:

Temporarily protects minor cuts, scrapes, and burns.

Helps prevent and temporarily protects chafed, chapped, or cracked skin.

Warnings:

- For external use only.
- Avoid contact with eyes. In case of contact, flush thoroughly with water.
- Do not use on deep or punctured wounds.
- Stop use and ask doctor if condition worsens
- symptoms last more than 7 days or clear up and occur again within a few days.

Warnings:

- Keep out of reach of children. In case of accidental ingestion contact a physician or Poison Control Center right away.

Directions:

Apply liberally to affected area as needed or as directed by physician.

Other Information:

- Store at room temperature (59°-86°F)
- You May report a serious adverse event to DermaRite Industries, PO Box 7209, North Bergen, NJ 07047.

Inactive Ingredients:

Cera Alba, Disodium EDTA, DMDM Hydantion, Lanolin Alcohol, Methylparaben, Mineral Oil, PEG-30 Dipolyhydroxydstearate, Petrolatum, Propylene Glycol, Propylparaben, Sodium Borate, Sodium Chloride, Water

Questions?

Call 1-800-337-6296 Mon-Fri 9AM-5PM EST.